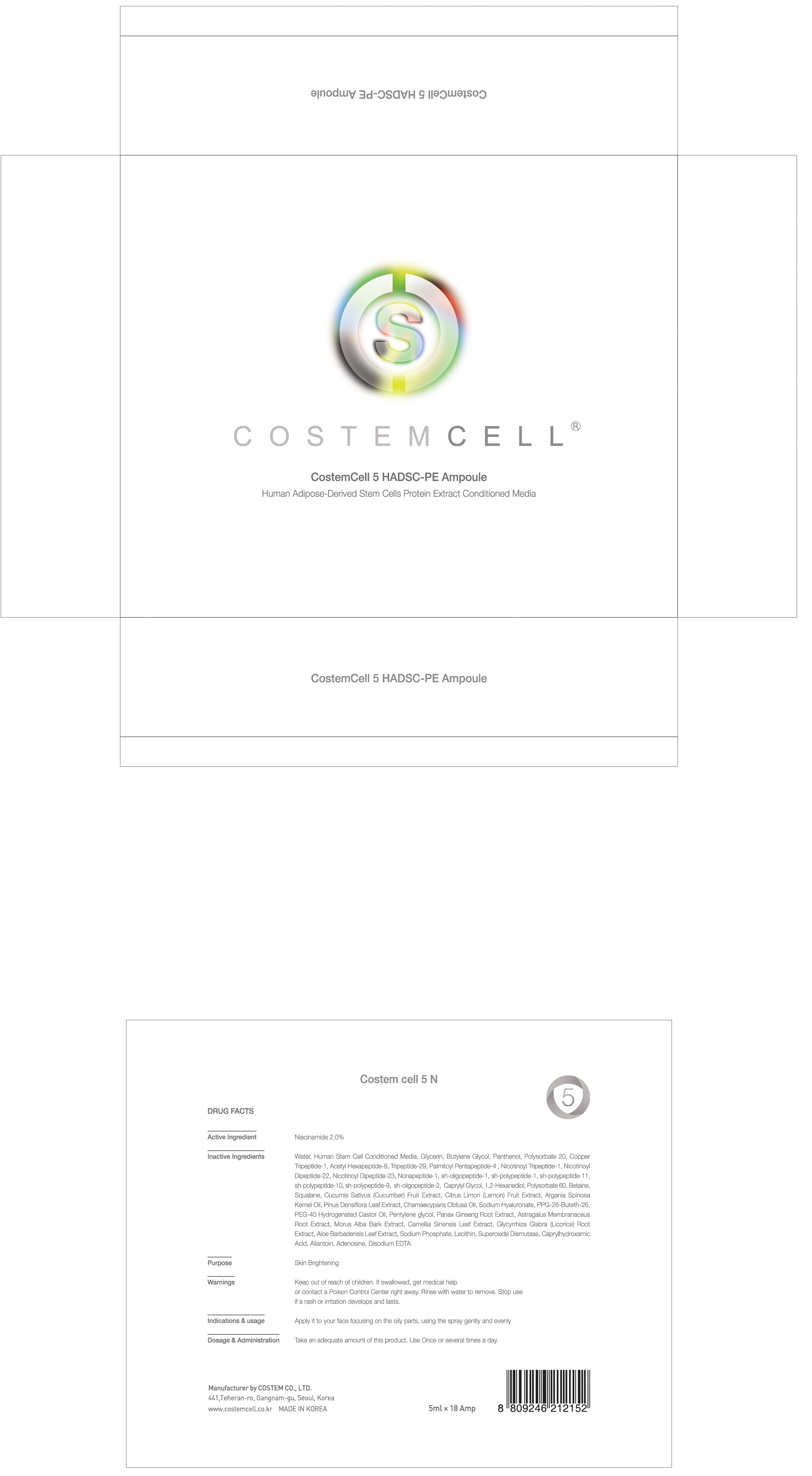 DRUG LABEL: Costem cell 5 N
NDC: 71044-010 | Form: SOLUTION
Manufacturer: COSTEMCELL.LTD.CO
Category: otc | Type: HUMAN OTC DRUG LABEL
Date: 20161117

ACTIVE INGREDIENTS: Niacinamide 0.1 g/5 mL
INACTIVE INGREDIENTS: Water; Glycerin

ACTIVE INGREDIENT

Active Ingredient: Niacinamide 2.0%

INACTIVE INGREDIENT

Inactive Ingredients: Water, Human Stem Cell Conditioned Media, Glycerin, Butylene Glycol, Panthenol, Polysorbate 20, Copper Tripeptide-1, Acetyl Hexapeptide-8, Tripeptide-29, Palmitoyl Pentapeptide-4 , Nicotinoyl Tripeptide-1, Nicotinoyl Dipeptide-22, Nicotinoyl Dipeptide-23, Nonapeptide-1, sh-oligopeptide-1, sh-polypeptide-1, sh-polypeptide-11, sh-polypeptide-10, sh-polypeptide-9, sh-oligopeptide-2, Caprylyl Glycol, 1,2-Hexanediol, Polysorbate 60, Betaine, Squalane, Cucumis Sativus (Cucumber) Fruit Extract, Citrus Limon (Lemon) Fruit Extract, Argania Spinosa Kernel Oil, Pinus Densiflora Leaf Extract, Chamaecyparis Obtusa Oil, Sodium Hyaluronate, PPG-26-Buteth-26, PEG-40 Hydrogenated Castor Oil, Pentylene glycol, Panax Ginseng Root Extract, Astragalus Membranaceus Root Extract, Morus Alba Bark Extract, Camellia Sinensis Leaf Extract, Glycyrrhiza Glabra (Licorice) Root Extract, Aloe Barbadensis Leaf Extract, Sodium Phosphate, Lecithin, Superoxide Dismutase, Caprylhydroxamic Acid, Allantoin, Adenosine, Disodium EDTA

PURPOSE

Purpose: Skin Brightening

WARNINGS

Warnings: Keep out of reach of children. If swallowed, get medical help or contact a Poison Control Center right away. Rinse with water to remove. Stop use if a rash or irritation develops and lasts.

KEEP OUT OF REACH OF CHILDREN

INDICATIONS & USAGE

Indications & usage: Apply it to your face focusing on the oily parts, using the spray gently and evenly

DOSAGE & ADMINISTRATION

Dosage & Administration: Take an adequate amount of this product. Use Once or several times a day.